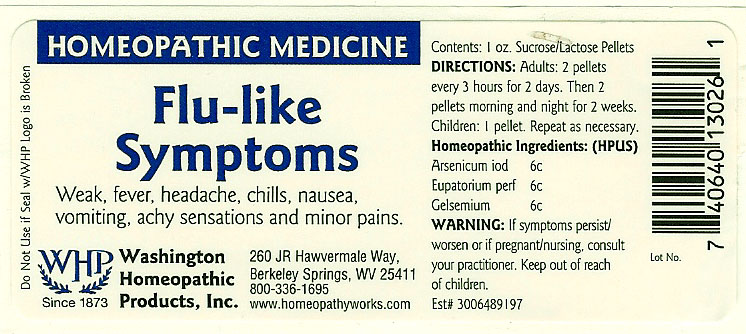 DRUG LABEL: Flu-like Symptoms
NDC: 68428-008 | Form: PELLET
Manufacturer: Washington Homeopathic Products
Category: homeopathic | Type: HUMAN OTC DRUG LABEL
Date: 20101021

ACTIVE INGREDIENTS: ARSENIC TRIIODIDE 6 [hp_C]/28 g; EUPATORIUM PERFOLIATUM FLOWERING TOP 6 [hp_C]/28 g; GELSEMIUM SEMPERVIRENS ROOT 6 [hp_C]/28 g
INACTIVE INGREDIENTS: SUCROSE; LACTOSE

DRUG FACTS

ACTIVE INGREDIENTS

ARSENICUM IOD 6C

EUPATORIUM PERF 6C

GELSEMIUM 6C

USES

To relieve the symptoms of weak, fever, headache, chills, nausea, vomiting, achy sensations and minor pains.

KEEP OUT OF REACH OF CHILDREN

Keep this and all medicines out of reach of children.

INDICATIONS

ARSENICUM IOD Lightheadedness

EUPATORIUM PERF Flu-like symptoms

GELSEMIUM Lethargy

STOP USE AND ASK DOCTOR

If symptoms persist/worsen or if pregnant/nursing, stop use and consult your practitioner.

DIRECTIONS

Adults 2 pellets every 3 hours for 2 days. Then 2 pellets morning and night for 2 weeks.

Children: 1 pellet. Repeat as necessary.

INACTIVE INGREDIENTS

Sucrose/Lactose

PRINCIPAL DISPLAY PANEL

Enter section text here